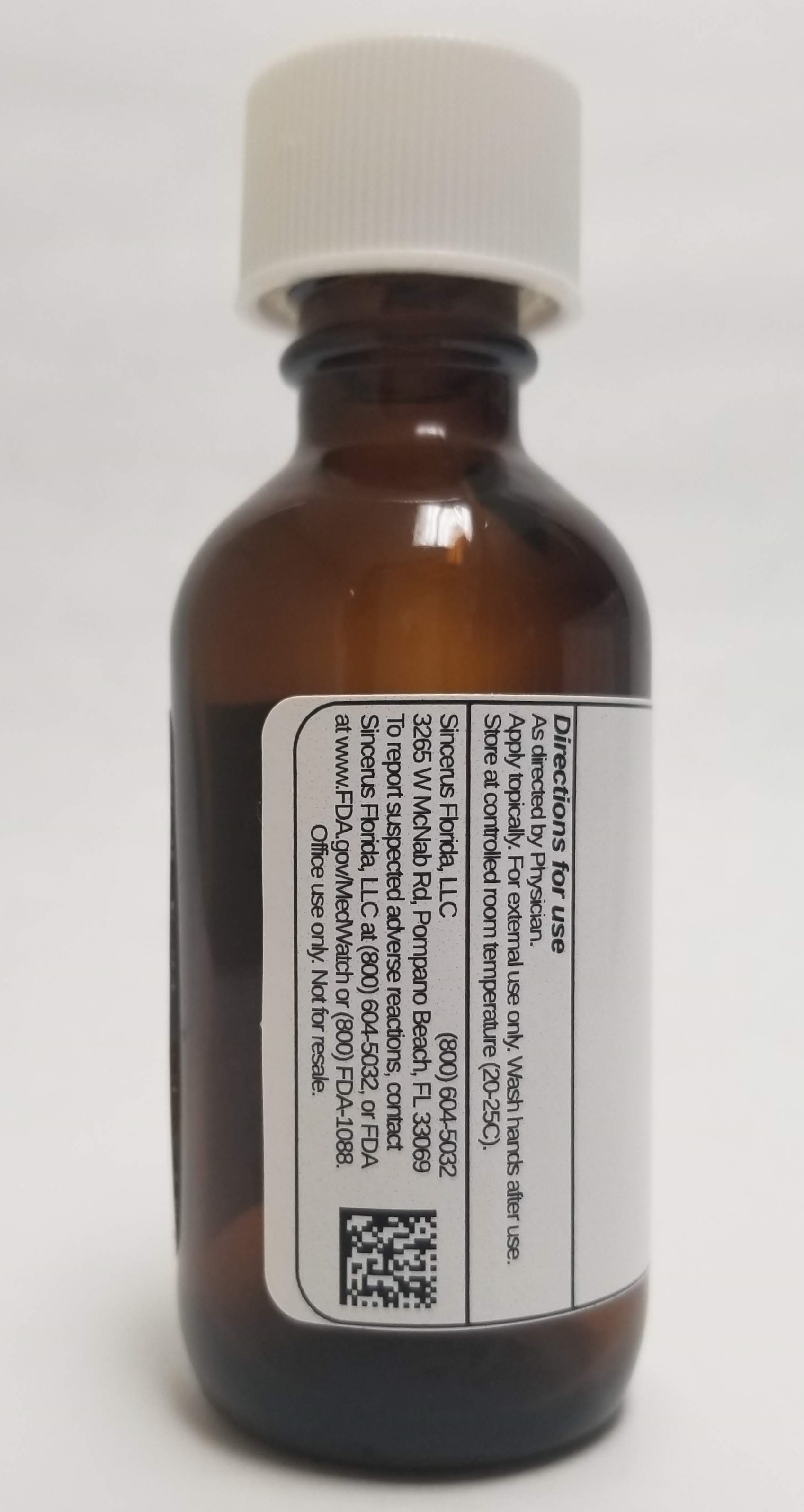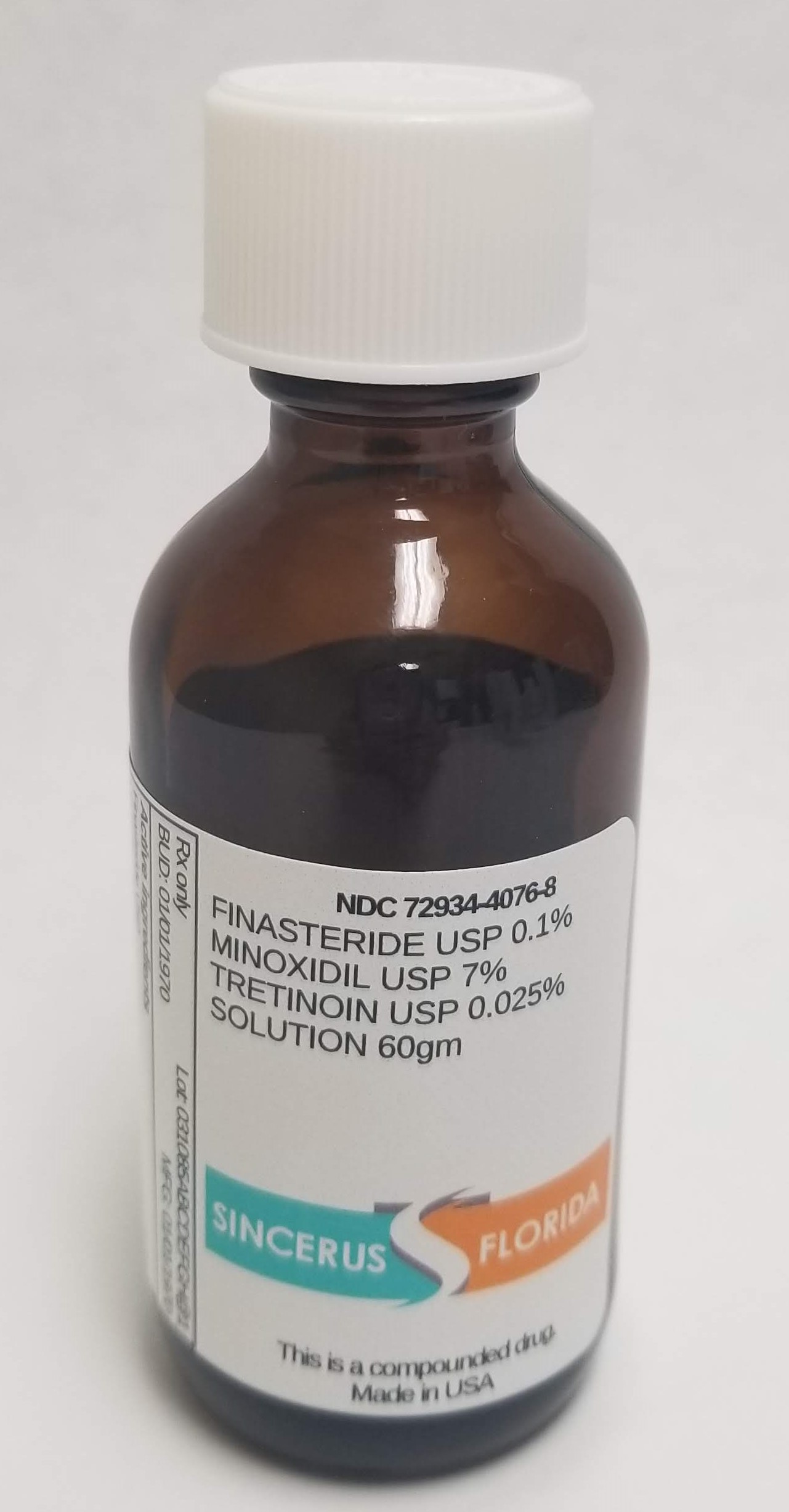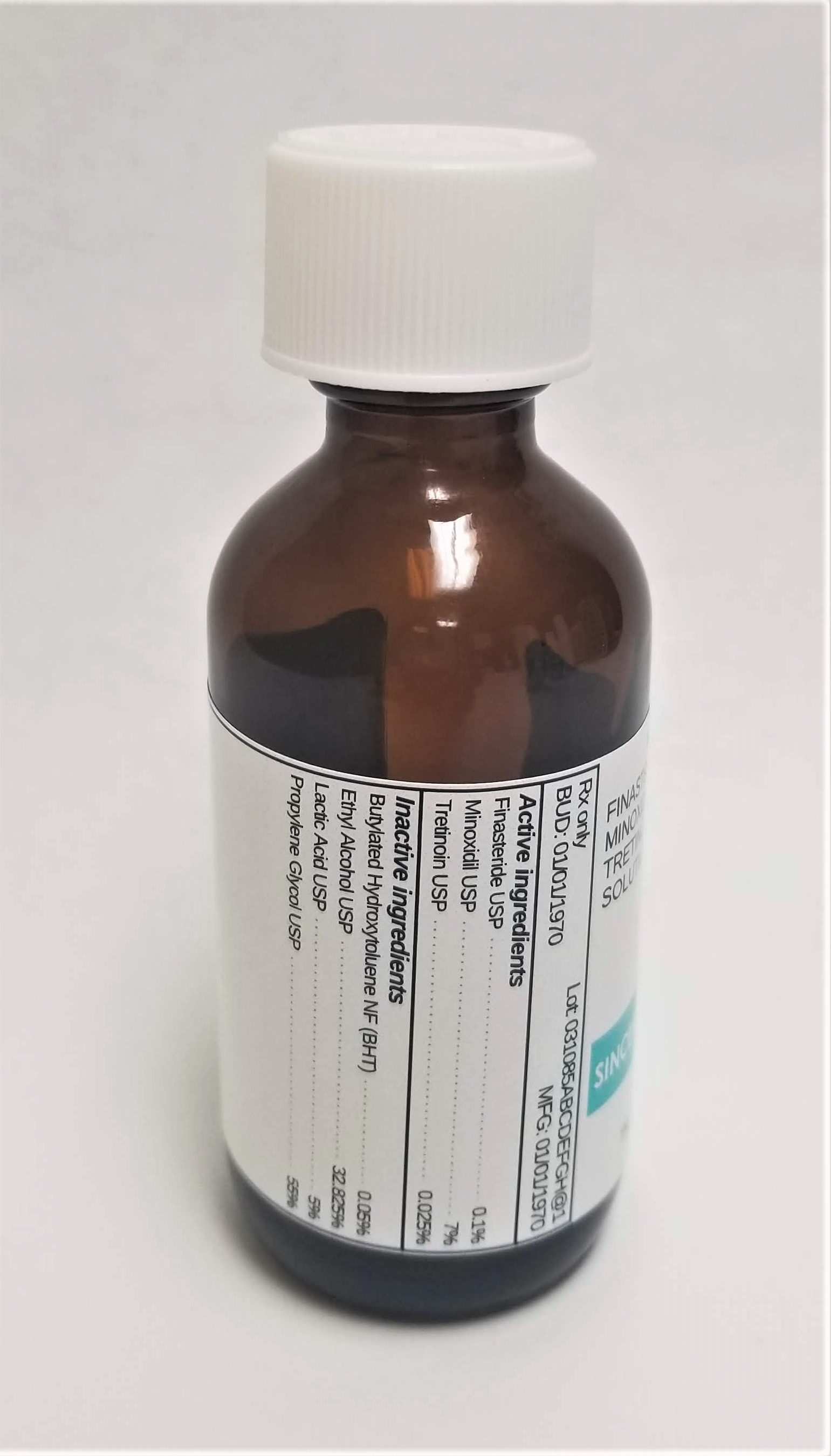 DRUG LABEL: FINASTERIDE 0.1% / MINOXIDIL 7% / TRETINOIN 0.025%
NDC: 72934-4076 | Form: SOLUTION
Manufacturer: Sincerus Florida, LLC
Category: prescription | Type: HUMAN PRESCRIPTION DRUG LABEL
Date: 20190510

ACTIVE INGREDIENTS: MINOXIDIL 7 g/100 g; FINASTERIDE 0.1 g/100 g; TRETINOIN 0.025 g/100 g

FINASTERIDE 0.1% / MINOXIDIL 7% / TRETINOIN 0.025%